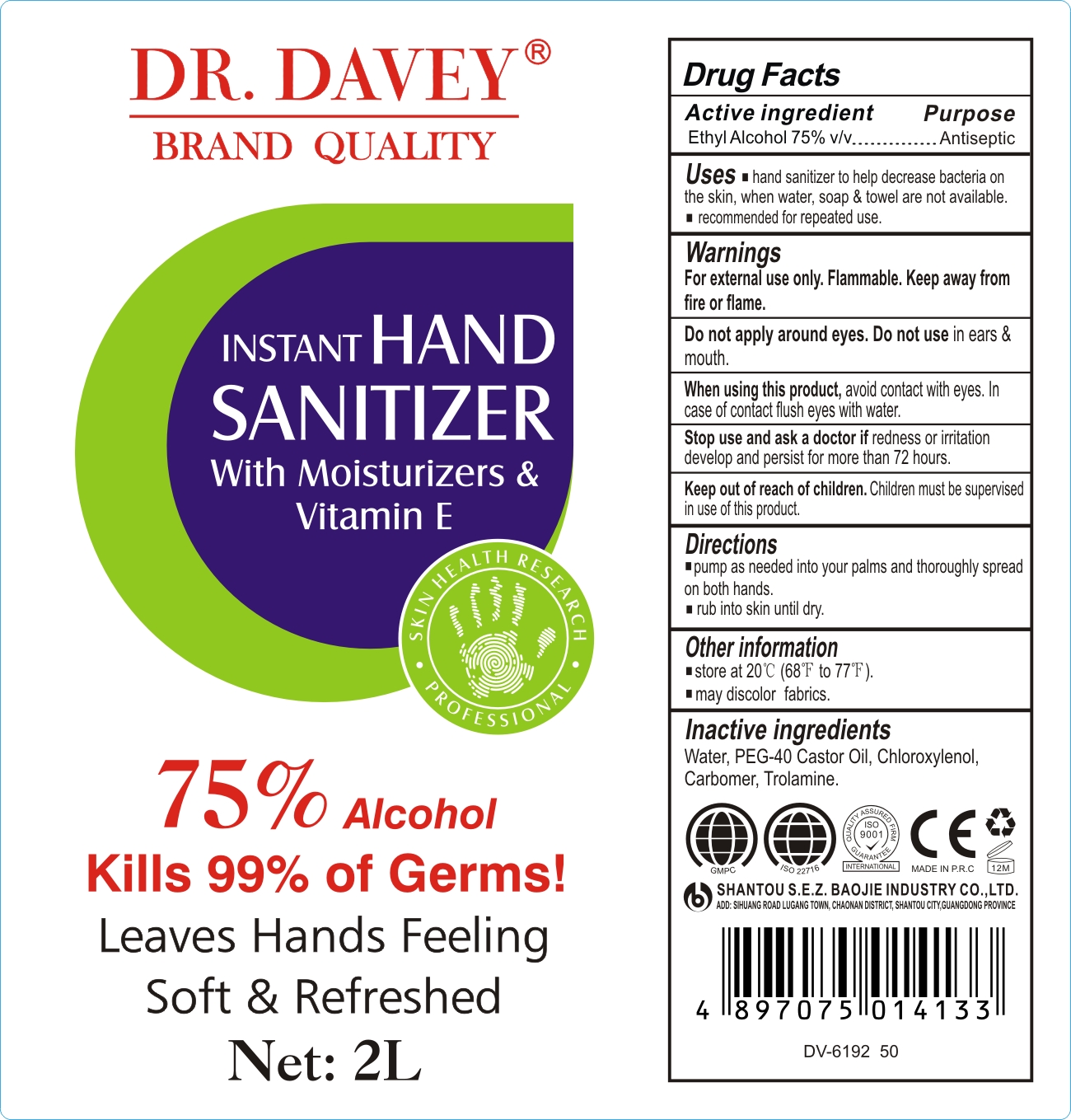 DRUG LABEL: Hand Sanitize
NDC: 74913-778 | Form: GEL
Manufacturer: SHANTOU S.E.Z BAOJIE INDUSTRY CO., LTD
Category: otc | Type: HUMAN OTC DRUG LABEL
Date: 20200508

ACTIVE INGREDIENTS: ALCOHOL 75 mL/100 mL
INACTIVE INGREDIENTS: CHLOROXYLENOL 0.3 mL/100 mL; CARBOMER 940 0.5 mL/100 mL; PEG-40 CASTOR OIL 0.5 mL/100 mL; TROLAMINE 0.5 mL/100 mL; WATER 23.2 mL/100 mL

HAND SANITIZER